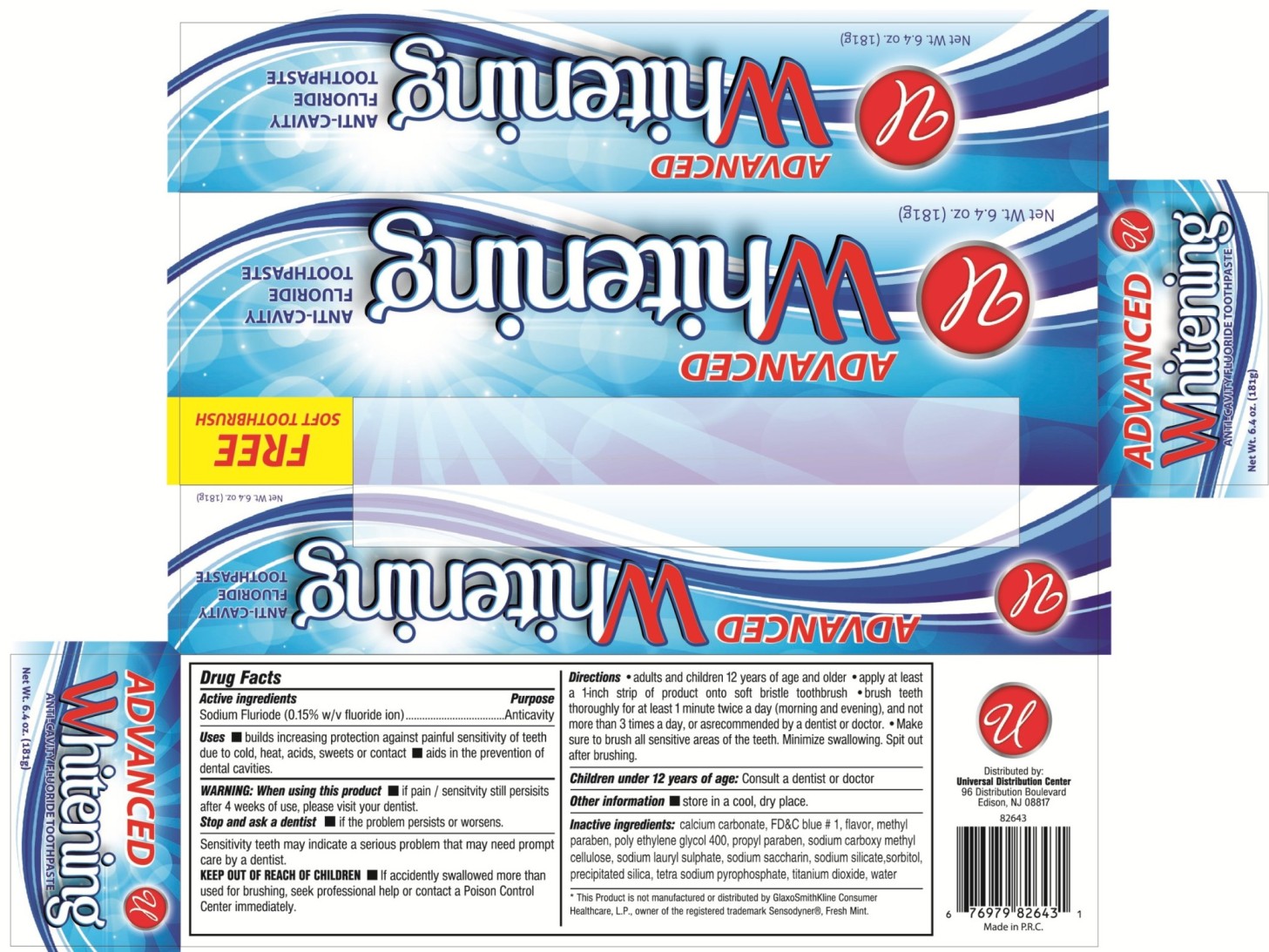 DRUG LABEL: ADVANCED WHITENING ANTI CAVITY FLUORIDE
NDC: 52000-035 | Form: PASTE
Manufacturer: Universal Distribution Center LLC
Category: otc | Type: HUMAN OTC DRUG LABEL
Date: 20170621

ACTIVE INGREDIENTS: SODIUM FLUORIDE 1.5 mg/1 g
INACTIVE INGREDIENTS: CALCIUM CARBONATE; FD&C BLUE NO. 1; METHYLPARABEN; POLYETHYLENE GLYCOL 400; PROPYLPARABEN; CARBOXYMETHYLCELLULOSE SODIUM, UNSPECIFIED FORM; SODIUM LAURYL SULFATE; SACCHARIN SODIUM; SODIUM SILICATE; SORBITOL; SODIUM PYROPHOSPHATE; TITANIUM DIOXIDE; WATER

ADVANCED WHITENING ANTI-CAVITY FLUORIDE TOOTHPASTE

Active Ingredient

Sodium Fluoride (0.15% w/v fluoride ion)

Purpose

Anticavity

Uses

- builds increasing protection against painful sensitivity of teeth due to cold, heat, acids, sweets or contact.
- aids in the prevention of dental cavities.

Warning

When using this product

- if pain\ sensitivity still persists after 4 weeks of use, please visit your dentist.

Stop and ask a dentist

- if the problem persists or worsens.

Sensitivity teeth may indicate a serious problem that may need prompt care by a dentist.

Keep out of reach of children

- If accidentally swallowed more than used for brushing, seek professional help or contact a Poison Control Center immediately.

Directions

Adults and Children 12 years of age and older:

- apply at least a 1-inch strip of product onto soft bristle toothbrush
- brush teeth thoroughly for at least 1 minute twice a day (morning and evening), and not more than 3 times day, or as recommended by a dentist or doctor.
- make sure to brush all sensitive areas of the teeth. Minimize swallowing. Spit out after brushing.

Children under 12 years of age: Consult a dentist or doctor.

Other information

- store in a cool, dry place.

Inactive Ingredients

calcium carbonate, FD&C blue#1, flavor, methylparaben, poly ethylene glycol 400, propylparaben, sodium carboxymethyl cellulose, sodium lauryl sulfate, sodium saccharin, sodium silicate, sorbitol, precipited silica, tetra sodium pyrophosphate, titanium dioxide, water.

PACKAGE LABEL

PRINCIPAL DISPLAY PANEL

ADVANCED WHITENING ANTI-CAVITY FLUORIDE TOOTHPASTE